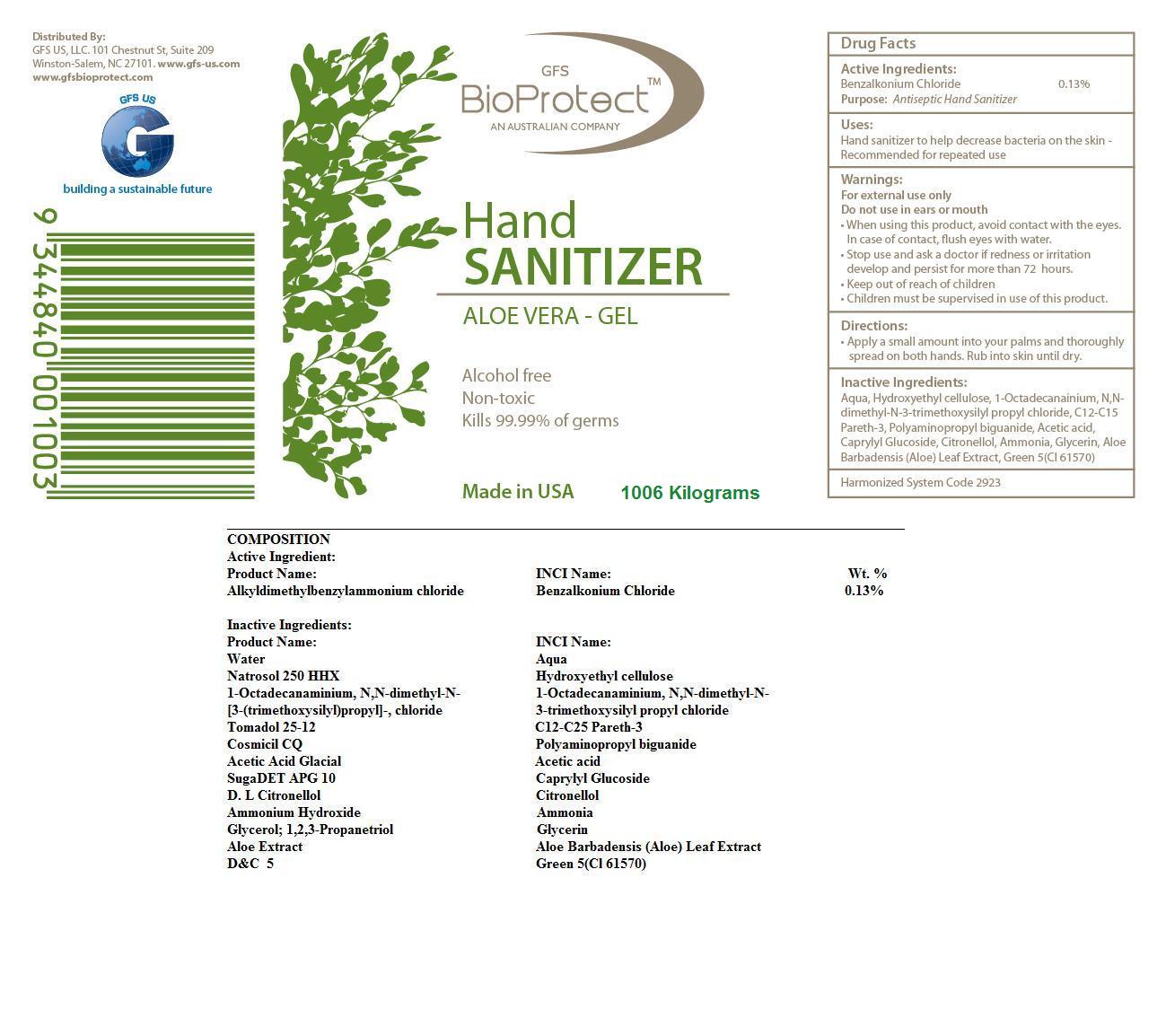 DRUG LABEL: GFS BioProtect  Aloe Vera Hand Sanitizer
NDC: 24673-712 | Form: GEL
Manufacturer: RWM TECHNOLOGIES
Category: otc | Type: HUMAN OTC DRUG LABEL
Date: 20110913

ACTIVE INGREDIENTS: Benzalkonium Chloride 0.0013 g/1 g
INACTIVE INGREDIENTS: Water 0.9532 g/1 g; HYDROXYETHYL CELLULOSE (4000 MPA.S FOR 1% AQUEOUS SOLUTION) 0.0155 g/1 g; DIMETHYLOCTADECYL(3-(TRIMETHOXYSILYL)PROPYL)AMMONIUM CHLORIDE 0.005 g/1 g; POLYAMINOPROPYL BIGUANIDE 0.005 g/1 g; Acetic Acid 0.003 g/1 g; CAPRYLYL GLUCOSIDE 0.003 g/1 g; .BETA.-CITRONELLOL, (+/-)- 0.003 g/1 g; AMMONIA 0.002 g/1 g; GLYCERIN 0.001 g/1 g; ALOE VERA LEAF 0.0005 g/1 g; D&C Green No. 5 0.0005 g/1 g

GFS BIOPROTECT ALOE VERA HAND SANITIZER-ALCOHOL FREE-GEL

DESCRIPTION

BioProtect Hand Sanitizer contains 0.13% antiseptic agent Benzalkonium Chloride formulated with Water,Hydroxyethyl Cellulose, Alkyl Polyglucoside, C12-C15 Pareth-3, 1-Ocatadecanaminium, N-N-dimethyl-N-[3-(trimethoxysilyl)propyl]-,chloride, Polyhexamethylene
Biguanide, Acetic Acid, Citronellol, Ammonia, Glycerin, Aloe Barbadensis (Aloe) Leaf Extract, and D and C Green No.5. It is alcohol-free, non-toxic and kills 99.99% of germs.

ACTIVE INGREDIENT

Benzalkonium Chloride 0.13%.............................................Antiseptic

PURPOSE

- Antispetic

INDICATIONS AND USAGE

- Hand sanitizer to help decrease bacteria on skin
- Recommended for repeated use

WARNINGS

- For external use only
- Do not use in ears or mouth

- Keep out of reach on children
- Children must be supervised in use of this product

DOSAGE AND ADMINISTRATION

- Apply a small amount into your palm and throughly spread on both hands
- Rub into skin until dry

GENERAL PRECAUTIONS

- Review MSDS before handling the product

- When using this product do not use in ears or mouth
- Avoid contact with eyes
- In case of eye contact, rinse eyes thoroughly with water

- Stop use and ask a doctor if skin irritation or redness develops and persists for more than 72 hours

INACTIVE INGREDIENT

Water; Hydroxyethyl Cellulose; Alkyl Polyglucoside; C12-C15 Pareth-3; 1-Ocatadecanaminium,
N-N-dimethyl-N-[3-(trimethoxysilyl)propyl]-,chloride; Polyhexamethylene Biguanide; Acetic Acid; Citronellol; Ammonia; Glycerin; Aloe
Barbadensis (Aloe) Leaf Extract; D and C Green No.5

Label